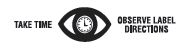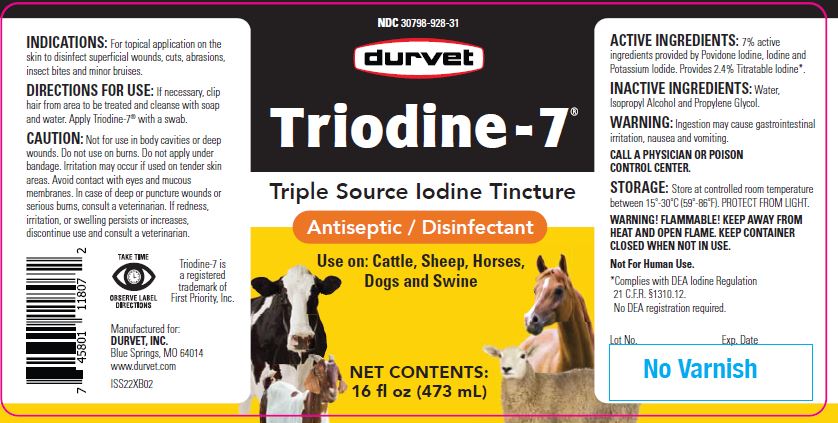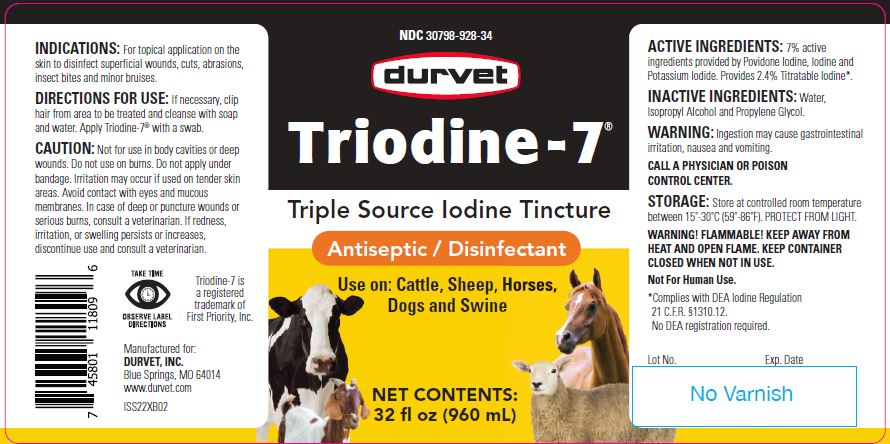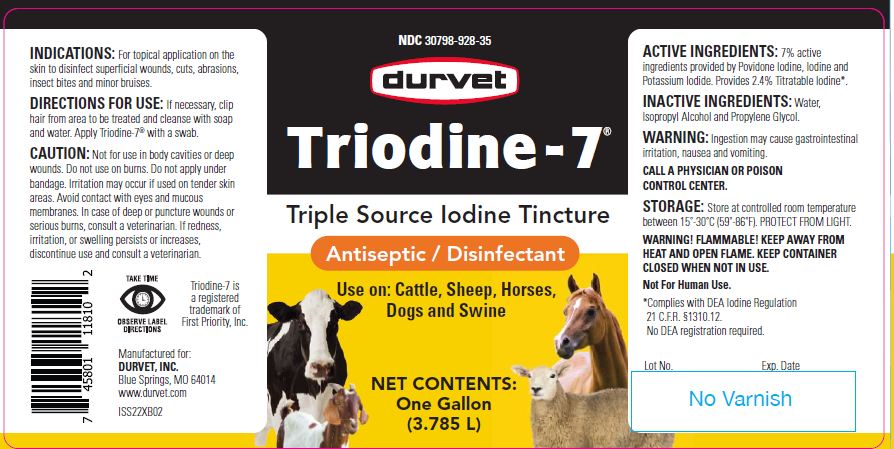 DRUG LABEL: Triodine
NDC: 30798-928 | Form: SOLUTION
Manufacturer: Durvet, Inc.
Category: animal | Type: OTC ANIMAL DRUG LABEL
Date: 20260223

ACTIVE INGREDIENTS: IODINE 2.1 mg/1 mL; POVIDONE-IODINE 3.0 mg/1 mL; POTASSIUM IODIDE 2.0 mg/1 mL

Triodine-7®

Triple Source Iodine Tincture

Antiseptic / Disinfectant

Use on: Cattle, Sheep, Horses, Dogs and Swine

INDICATIONS:

For topical application on the skin to disinfect superficial wounds, cuts, abrasions, insect bites and minor bruises.

DIRECTIONS FOR USE:

If necessary, clip hair from area to be treated and cleanse with soap and water. Apply Triodine-7® with a swab.

CAUTION:

Not for use in body cavities or deep wounds. Do not use on burns. Do not apply under bandage. Irritation may occur if used on tender skin areas. Avoid contact with eyes and mucous membranes. In case of deep or puncture wounds or serious burns, consult a veterinarian. If redness, irritation, or swelling persists or increases, discontinue use and consult a veterinarian.

WARNINGS

Triodine-7 is a registered trademark of First Priority, Inc.

Manufactured for:
DURVET, INC.
Blue Springs, MO 64014
www.durvet.com

ACTIVE INGREDIENTS:

7% active ingredients provided by Povidone Iodine, Iodine and Potassium Iodide. Provides 2.4% Titratable Iodine*.

INACTIVE INGREDIENTS:

Water, Isopropyl Alcohol and Propylene Glycol.

WARNING:

Ingestion may cause gastrointestinal irritation, nausea and vomiting.

CALL A PHYSICIAN OR POISON CONTROL CENTER.

STORAGE:

Store at controlled room temperature between 15°-30°C (59°-86°F). PROTECT FROM LIGHT.

WARNINGS AND PRECAUTIONS

WARNING! FLAMMABLE! KEEP AWAY FROM HEAT AND OPEN FLAME. KEEP CONTAINER CLOSED WHEN NOT IN USE.
Not For Human Use.

*Complies with DEA Iodine Regulation 21 C.F.R. §1310.12.
No DEA registration required.

NET CONTENTS:

16 fl oz (473 mL)

32 fl oz (960 mL)

One Gallon (3.785 L)